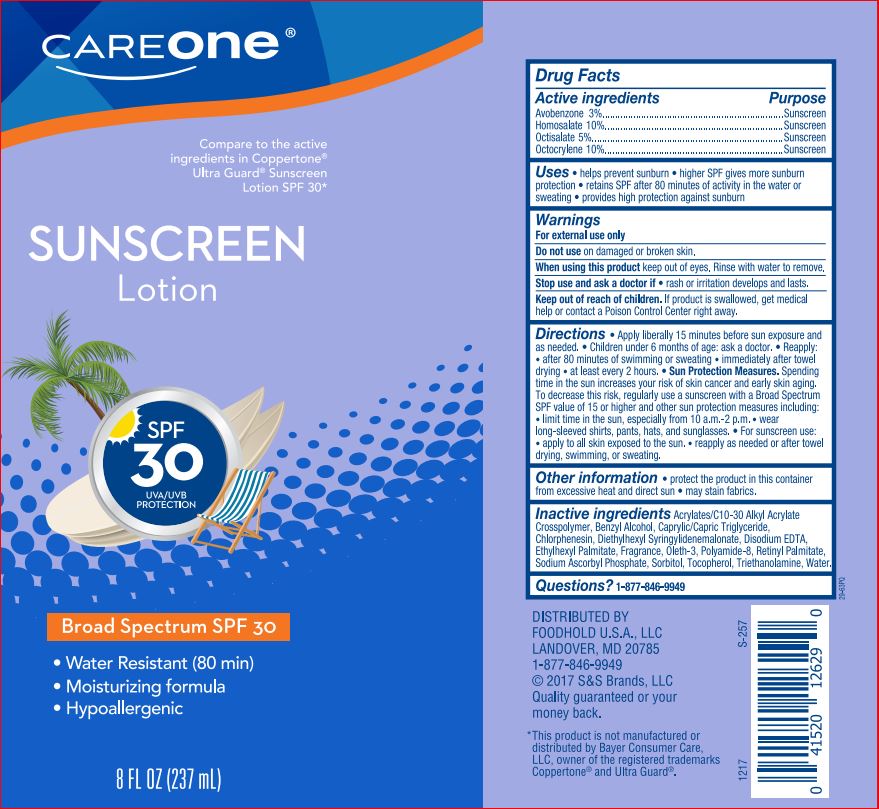 DRUG LABEL: Sunscreen SPF 30
NDC: 41520-347 | Form: LOTION
Manufacturer: CareOne
Category: otc | Type: HUMAN OTC DRUG LABEL
Date: 20180716

ACTIVE INGREDIENTS: AVOBENZONE 3 g/100 mL; HOMOSALATE 10 g/100 mL; OCTISALATE 5 g/100 mL; OCTOCRYLENE 10 g/100 mL
INACTIVE INGREDIENTS: CARBOMER COPOLYMER TYPE B (ALLYL PENTAERYTHRITOL CROSSLINKED); BENZYL ALCOHOL; MEDIUM-CHAIN TRIGLYCERIDES; CHLORPHENESIN; DIETHYLHEXYL SYRINGYLIDENEMALONATE; EDETATE DISODIUM; ETHYLHEXYL PALMITATE; OLETH-3; NEOPENTYL GLYCOL; VITAMIN A PALMITATE; SODIUM ASCORBYL PHOSPHATE; SORBITOL; TOCOPHEROL; TROLAMINE

Drug Facts

Actives

Avobenzone 3.0%

Homosalate 10.0%

Octisalate 5.0%

Octocrylene 10.0%

Purpose

Sunscreen

Uses

- helps prevent sunburn • Higher SPF gives more sunburn protection•retains SPF after 80 minutes of activity in the weater or sweating • provides hight protection against sunburn

Warnings

For external use only

Do not use

on damaged or broken skin

When using this product

keep out of eyes. Rinse with water to remove.

Stop use and ask a doctor

if rash or irritation develops and lasts

Keep out of reach of children.

If product is swallowed, get medical help or contact a Poison Control Center right away.

Directions

- apply liberally 15 minutes before sun exposure
- Reapply: • After 80 minutes of swimming or sweating • Immediately after towel drying • At least every 2 hours
- Sun Protection Measures. Spending time in the sun increases your risk of skin cancer and early skin aging. To decrease this risk, regularly use a sunscreen with a broad spectrum SPF of 15 or higher and other sun protection measure including: • limit time in the sun, especially from 10 a.m. – 2 p.m • wear long-sleeve shirts, pants, hats, and sunglasses
- children under 6 months: Ask a doctor

Inactive Ingredients

Acrylates/C10-30 Alkyl Acrylate Crosspolymer, Benzyl Alcohol, Caprylic/Capric Triglyceride, Chlorphenesin, Diethylhexyl Syringylidemaionate, Disodium EDTA, Ethylhexyl Palmitate, Fragrance, Oieth-3, Polyamide-8, Retinyl Palmitate, Sodium Ascorbyl Phosphate, Sorbitol, Tocopherol, Triethanolamine, Water.